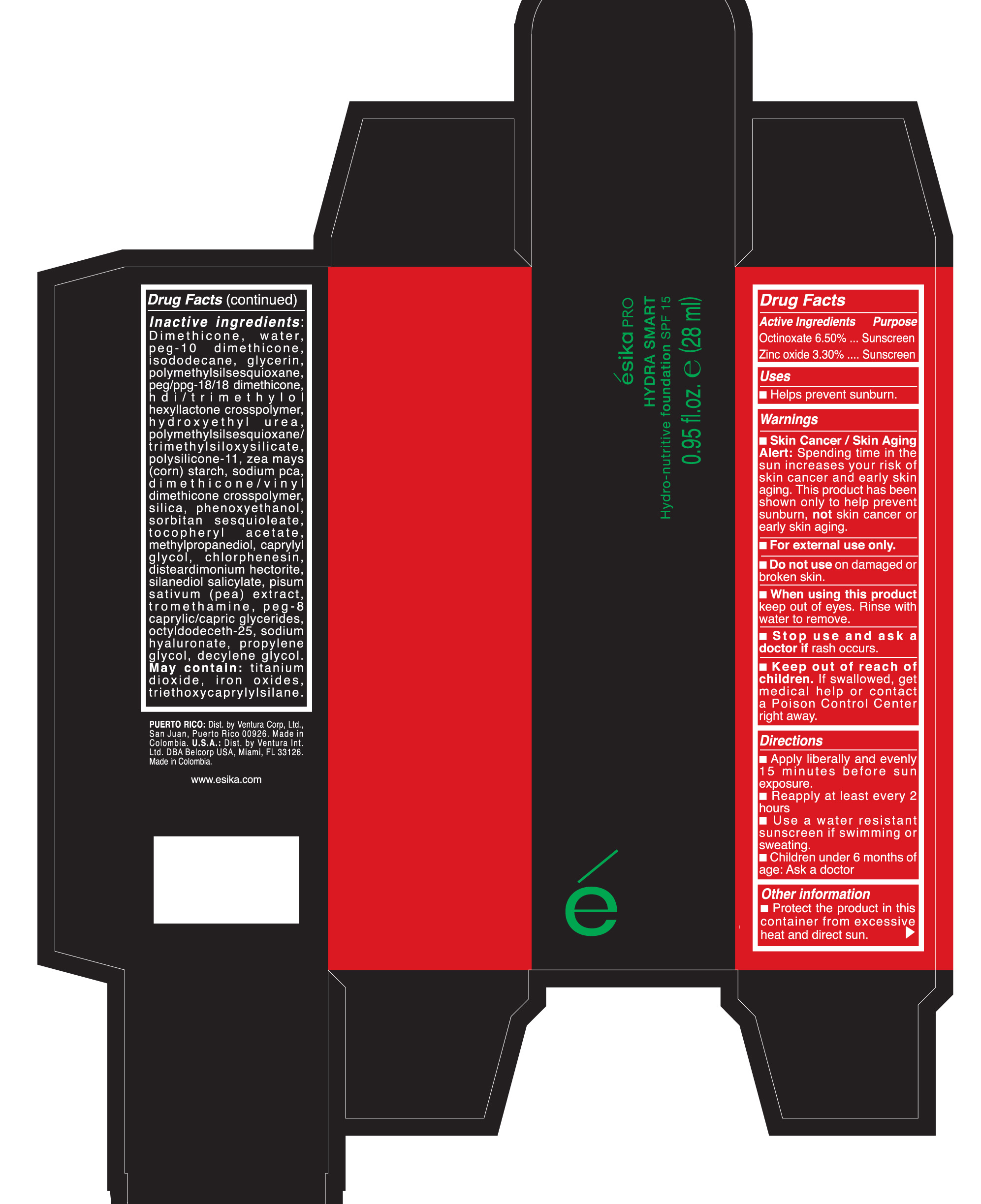 DRUG LABEL: Esika Pro Hydra Smart Hydro-nutritive foundation SPF 15
NDC: 43596-0136 | Form: CREAM
Manufacturer: Ventura Corporation Limited
Category: otc | Type: HUMAN OTC DRUG LABEL
Date: 20191210

ACTIVE INGREDIENTS: OCTINOXATE 0.065 g/1 mL; ZINC OXIDE 0.33 g/1 mL
INACTIVE INGREDIENTS: GLYCERIN; SILICON DIOXIDE; CHLORPHENESIN; DISTEARDIMONIUM HECTORITE; SILANEDIOL SALICYLATE; PEA; PEG-10 DIMETHICONE (600 CST); .ALPHA.-TOCOPHEROL ACETATE; POLYMETHYLSILSESQUIOXANE (4.5 MICRONS); HEXAMETHYLENE DIISOCYANATE/TRIMETHYLOL HEXYLLACTONE CROSSPOLYMER; FERROSOFERRIC OXIDE; TRIETHOXYCAPRYLYLSILANE; FERRIC OXIDE RED; FERRIC OXIDE YELLOW; PHENOXYETHANOL; TITANIUM DIOXIDE; ISODODECANE; HYDROXYETHYL UREA; STARCH, CORN; CAPRYLOCAPROYL POLYOXYLGLYCERIDES 8; TROMETHAMINE; OCTYLDODECETH-25; HYALURONATE SODIUM; PROPYLENE GLYCOL; DECYLENE GLYCOL; DIMETHICONE 100; WATER; METHYLPROPANEDIOL; SODIUM PYRROLIDONE CARBOXYLATE; DIMETHICONE/VINYL DIMETHICONE CROSSPOLYMER (SOFT PARTICLE); CAPRYLYL GLYCOL; SORBITAN SESQUIOLEATE; PEG/PPG-18/18 DIMETHICONE

Esika Pro Hydra Smart Hydro-nutritive foundation SPF 15

Active Ingredients Purpose

Avobezone 1.80% Sunscreen

Octocrylene 4.5% Sunscreen

Octisalate 4.5% Sunscreen

Uses

- Helps prevent sunburn

Keep out of reach of children. If product is swallowed, get medical help or
contact a Poison Control Center right away.

Stop use and ask a doctor if rash occurs

Warnings

Skin Cancer/Skin Aging Alert: Spending time in the sun increases your risk of skin cancer and early skin aging. This product has been shown only to help sunburn, not skin cancer or early skin aging.

For external use only.

When using this product keep out of eyes. Rinse with water to remove

DOSAGE AND ADMINISTRATION

- Apply liberally 15 minutes before sun exposure
- Reapply at least every 2 hours
- Use a water resistant sunscreen if swimming or sweating
- Children under 6 months of age: Ask a doctor.

Inactive ingredients:

Dimethicone, water, PEG-10 dimethicone, isododecane, glycerin, polymethylsilsesquioxane, peg/ppg-18/18 dimethicone, hdi/trimethylol hexyllactone crosspolymer, hydroxyethyl urea, polymethylsilsesquioxane/trimethylsiloxysilicate, polysilicone-11, Zea Mays (corn) starch, sodium pca, dimethicone/vinyl dimethicone crosspolymer, silica, phenoxyethanol, sorbitan sesquioleate, tocopheryl acetate, methylpropanediol, caprylyl glycol, chlorphenesin, disteardimonium hectorite, silanediol salicylate, pisum sativum (pea) extract extract, tromethamine, peg-8 caprylic/capric glycerides, octyldodeceth-25, sodium hyaluronate, propylene glycol, decylene.

May contain titanium, iron oxides, triethoxycaprylylsilane

PACKAGE LABEL

Esika Pro

HYDRA SMART

hydra-nutritive foundation SPF 15

0.95 fl oz e (28 ml)